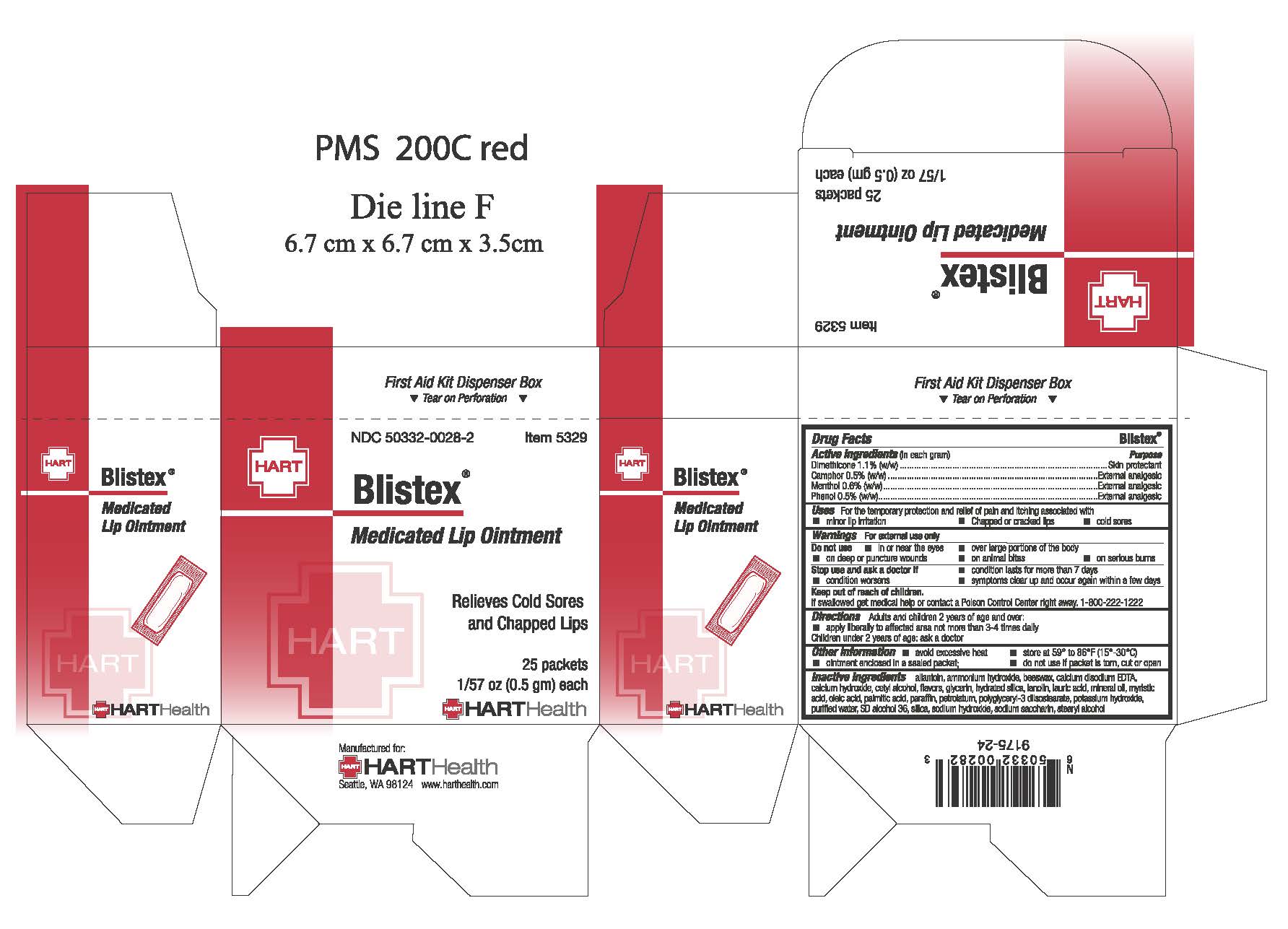 DRUG LABEL: Blistex Lip
NDC: 50332-0028 | Form: OINTMENT
Manufacturer: HART Health
Category: otc | Type: HUMAN OTC DRUG LABEL
Date: 20240118

ACTIVE INGREDIENTS: DIMETHICONE 1.1 g/100 g; CAMPHOR OIL .5 g/100 g; MENTHOL .6 g/100 g; PHENOL .5 g/100 g
INACTIVE INGREDIENTS: ALLANTOIN; EDETATE CALCIUM DISODIUM; CALCIUM HYDROXIDE; CETYL ALCOHOL; GLYCERIN; LANOLIN; LAURIC ACID; MINERAL OIL; MYRISTIC ACID; OLEIC ACID; PALMITIC ACID; PARAFFIN; PETROLATUM; POLYGLYCERYL-3 DIISOSTEARATE; POTASSIUM HYDROXIDE; WATER; SODIUM HYDROXIDE; STEARYL ALCOHOL

BLISTEX LIP OINTMENT

Active Ingredients:

Dimethicone 1.1% (w/w)

Camphor 0.5% (w/w)

Menthol 0.6% (w/w)

Phenol 0.5% (w/w)

Purpose:

Skin protectant

External analgesic

External analgesic

External analgesic

INDICATIONS AND USAGE

Uses: for the temporary protection and relief of pain and itching associated with

- minor lip irritation
- chapped or cracked lips
- cold sores

Warnings: For external use only

Do not use

- in the eyes or over large portions of the body
- on deep or puncture wounds
- on animal bites
- on serious burns

Stop use and ask a doctor if

- condition worsens
- condition lasts for more than 7 days
- symptoms clear up and occur again within a few days

Keep out of reach of children. If swallowed, get medical help or contact a Poison Control Center right away. 1-800-222-1222

Directions

Adults and children 2 years of age and over: apply liberally to affected area not more than 3 to 4 times daily

Children under 2 years of age: ask a doctor

INACTIVE INGREDIENT

Inactive Ingredients: Allontoin, Ammonium Hydroxide, Beeswax, Calcium Disodium EDTA, Calcium Hydroxide, Cetyl Alcohol, Flavors, Glycerin, Lanolin, Lauric Acid, Mineral Oil, Myristic Acid, Oleic Acid, Palmitic Acid, Paraffin, Petrolatum, Polyglyceryl-3 diisostearate, Potassium Hydroxide, Purified Water, SD Alcohol 36, Silica, Sodium Hydroxide, Sodium Saccharin, Stearyl Alcohol